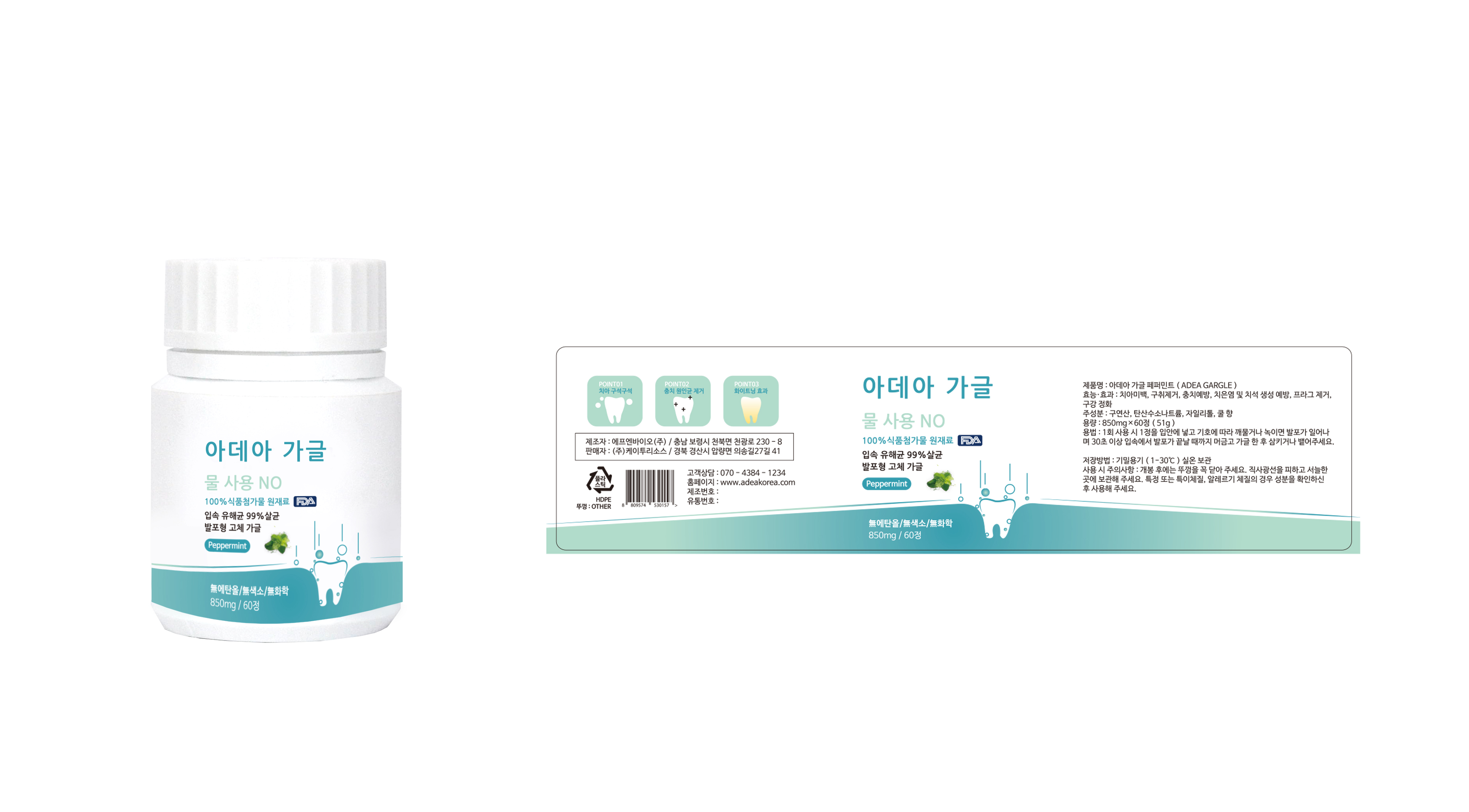 DRUG LABEL: ADEA GARGLE
NDC: 72191-0100 | Form: TABLET, CHEWABLE
Manufacturer: K2resource co., ltd.
Category: otc | Type: HUMAN OTC DRUG LABEL
Date: 20180326

ACTIVE INGREDIENTS: SODIUM BICARBONATE 36.2 g/100 mg; XYLITOL 5 g/100 mg
INACTIVE INGREDIENTS: MENTHOL

ACTIVE INGREDIENT

CITRIC ACID, SODIUM HYDROGEN CARBONATE, XYLITOL

PURPOSE

For oral care: Tooth whitening, removing bad breath, preventing tooth decay, preventing gingivitis and tartar formation, plaque removal, oral cleansing

Keep out of reach of children

INDICATIONS AND USAGE

Put a tablet of Adea Gargle in your mouth and chew or melt according to your preference.

When foaming starts, please gaggle for more than 30 seconds so that every corner of the mouth can reach Adea Gaggle.

When the gaggle is over, spit or swallow the bubbles.

WARNINGS

Airtight container

Storage at room temperature

Please close the lid tightly after opening.

Avoid direct sunlight and store in a cool place.

For specific or unusual constitution, allergic constitution, please use after checking ingredients.

INACTIVE INGREDIENT

GLUCOSE, MENTHOL, MAGNESIUM STEARATE, ASPARTAME, SUCRALOSE

DOSAGE AND ADMINISTRATION

For dental use only